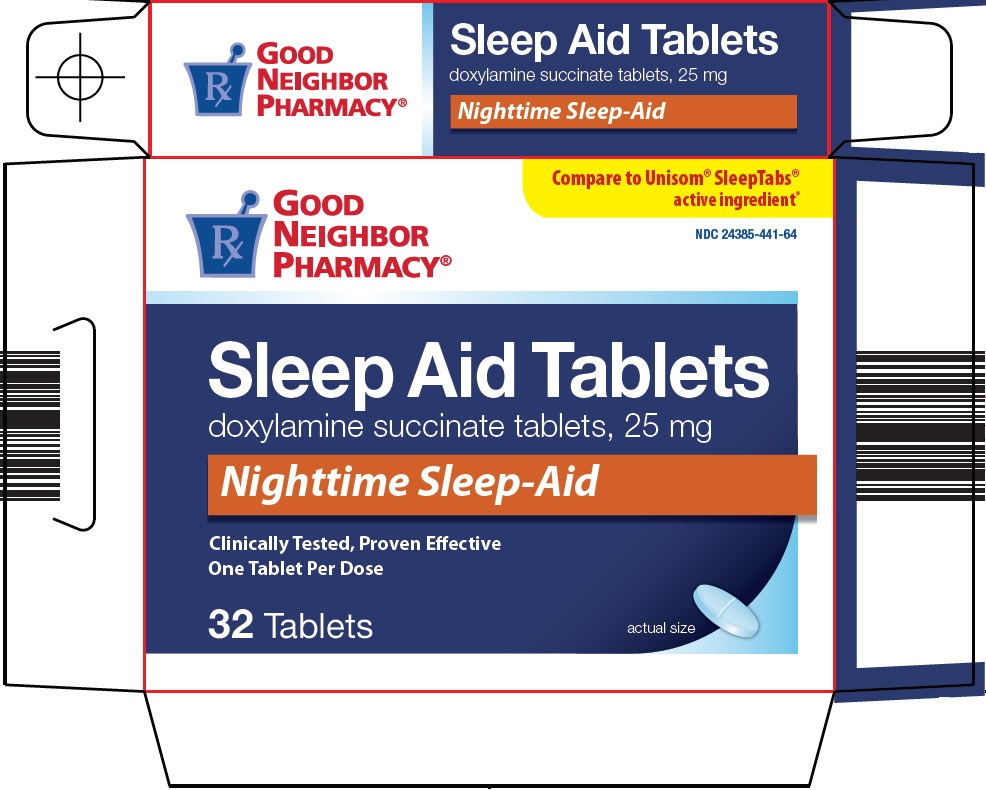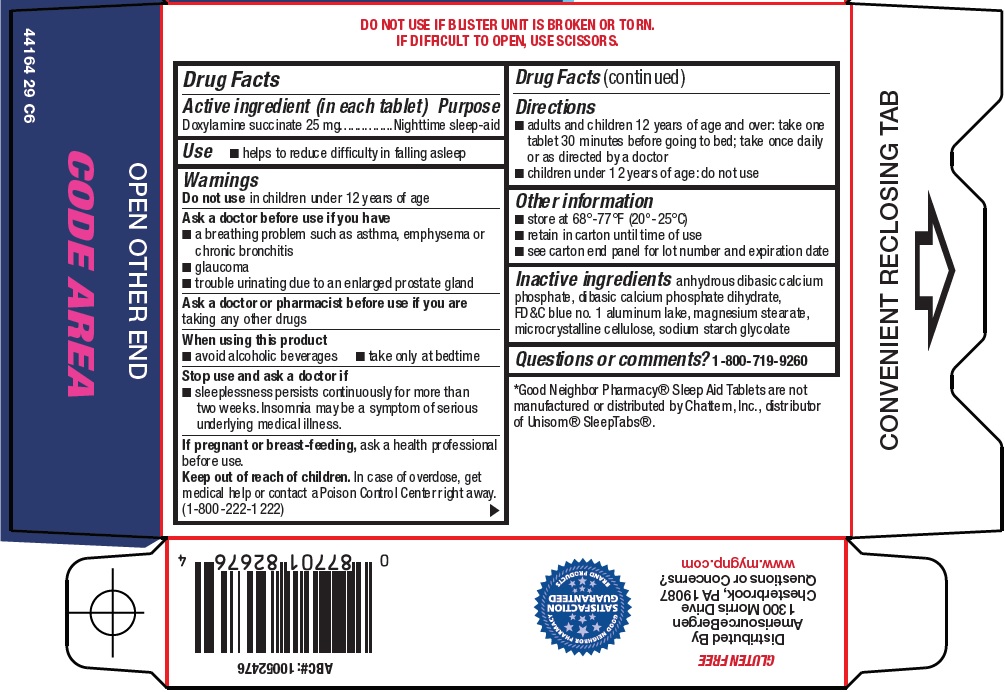 DRUG LABEL: Good Neighbor Pharmacy Sleep Aid
NDC: 24385-441 | Form: TABLET
Manufacturer: Amerisource Bergen
Category: otc | Type: HUMAN OTC DRUG LABEL
Date: 20240809

ACTIVE INGREDIENTS: DOXYLAMINE SUCCINATE 25 mg/1 1
INACTIVE INGREDIENTS: MAGNESIUM STEARATE; MICROCRYSTALLINE CELLULOSE; ANHYDROUS DIBASIC CALCIUM PHOSPHATE; DIBASIC CALCIUM PHOSPHATE DIHYDRATE; FD&C BLUE NO. 1

Amerisource Bergen Sleep Aid Tablets Drug Facts

Active ingredient (in each tablet)

Doxylamine succinate 25 mg

Purpose

Nighttime sleep-aid

Use

- helps to reduce difficulty in falling asleep

Warnings

Do not use

in children under 12 years of age

Ask a doctor before use if you have

- a breathing problem such as asthma, emphysema or chronic bronchitis
- glaucoma
- trouble urinating due to an enlarged prostate gland

Ask a doctor or pharmacist before use if you are

taking any other drugs

When using this product

- avoid alcoholic beverages
- take only at bedtime

Stop use and ask a doctor if

- sleeplessness persists continuously for more than two weeks. Insomnia may be a symptom of serious underlying medical illness.

If pregnant or breast-feeding,

ask a health professional before use.

Keep out of reach of children.

In case of overdose, get medical help or contact a Poison Control Center right away. (1-800-222-1222)

Directions

- adults and children 12 years of age and over: take one tablet 30 minutes before going to bed; take once daily or as directed by a doctor
- children under 12 years of age: do not use

Other information

- store at 68°-77°F (20°-25°C)
- retain in carton until time of use
- see carton end panel for lot number and expiration date

Inactive ingredients

anhydrous dibasic calcium phosphate, dibasic calcium phosphate dihydrate, FD&C blue no. 1 aluminum lake, magnesium stearate, microcrystalline cellulose, sodium starch glycolate

Questions or comments?

1-800-719-9260

Principal Display Panel

Compare to Unisom® SleepTabs® active ingredient

Sleep Aid Tablets

doxylamine succinate tablets, 25 mg

Nighttime Sleep-Aid

Clinically Tested, Proven Effective

One Tablet Per Dose

32 Tablets

actual size